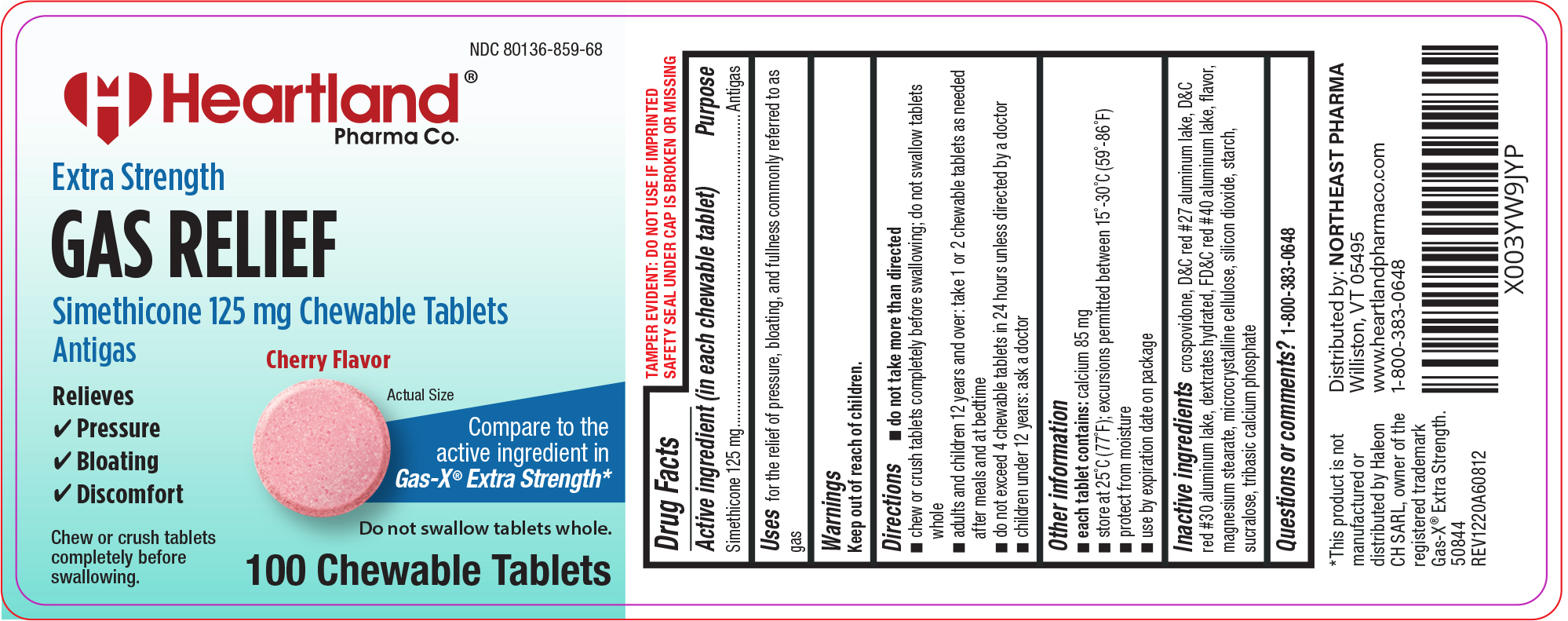 DRUG LABEL: Gas Relief
NDC: 80136-859 | Form: TABLET, CHEWABLE
Manufacturer: Heartland Pharma Co.
Category: otc | Type: HUMAN OTC DRUG LABEL
Date: 20251003

ACTIVE INGREDIENTS: DIMETHICONE 125 mg/1 1
INACTIVE INGREDIENTS: CROSPOVIDONE, UNSPECIFIED; D&C RED NO. 27 ALUMINUM LAKE; D&C RED NO. 30 ALUMINUM LAKE; DEXTROSE MONOHYDRATE; FD&C RED NO. 40 ALUMINUM LAKE; MAGNESIUM STEARATE; MICROCRYSTALLINE CELLULOSE; SILICON DIOXIDE; STARCH, CORN; SUCRALOSE; TRIBASIC CALCIUM PHOSPHATE; DIMETHICONE 410

Heartland Pharma 44-608

Active ingredient (in each chewable tablet)

Simethicone 125 mg

Purpose

Antigas

Uses

for the relief of pressure, bloating, and fullness commonly referred to as gas

Directions

- do not take more than directed
- chew or crush tablets completely before swallowing; do not swallow tablets whole
- adults and children 12 years and over: take 1 or 2 chewable tablets as needed after meals and at bedtime
- do not exceed 4 chewable tablets in 24 hours unless directed by a doctor
- children under 12 years: ask a doctor

Other information

- each tablet contains: calcium 85 mg
- store at 25°C (77°F); excursions permitted between 15°-30°C (59°-86°F)
- protect from moisture
- use by expiration date on package

Inactive ingredients

crospovidone, D&C red #27 aluminum lake, D&C red #30 aluminum lake, dextrates hydrated, FD&C red #40 aluminum lake, flavor, magnesium stearate, microcrystalline cellulose, silicon dioxide, starch, sucralose, tribasic calcium phosphate

Questions or comments?

1-800-383-0648

Principal display panel

Heartland®
Pharma Co.

NDC 80136-859-68

Extra Strength
GAS RELIEF
Simethicone 125 mg Chewable Tablets
Antigas

Relieves
Pressure
Bloating
Discomfort

Compare to the
active ingredient in
Gas-X® Extra Strength*

Chew or crush tablets completely before swallowing.

100 Chewable Tablets

Actual
Size

TAMPER EVIDENT: DO NOT USE IF IMPRINTED
SAFETY SEAL UNDER CAP IS BROKEN OR MISSING

*This product is not manufactured or distributed by Haleon CH SARL, owner of the registered trademark
Gas-X® Extra Strength.

50844 REV1220A60812

Distributed by:
NORTHEAST PHARMA
Williston, VT 05495
www.heartlandpharmaco.com
1-800-383-0648

44-608